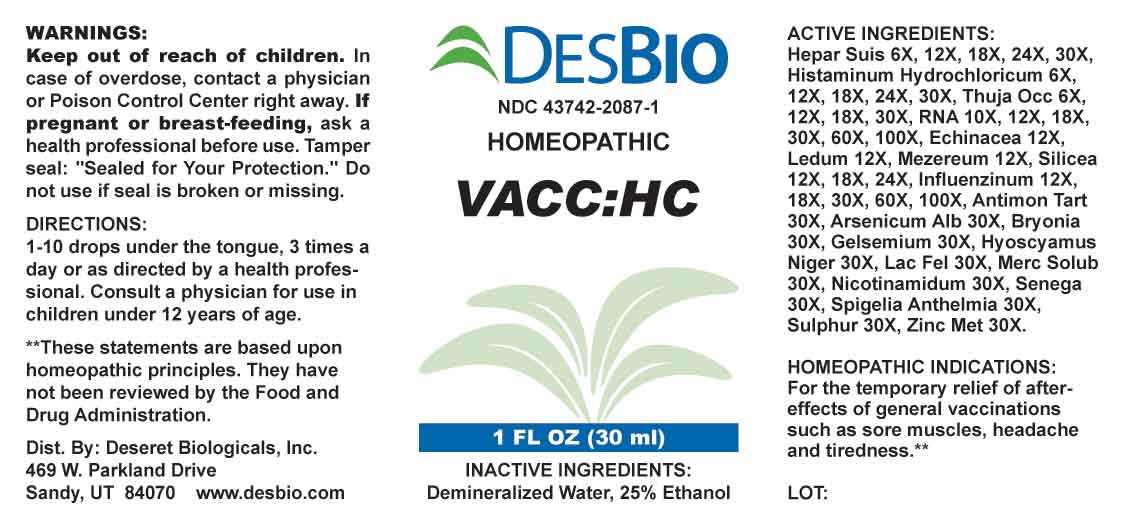 DRUG LABEL: VACC HC
NDC: 43742-2087 | Form: LIQUID
Manufacturer: Deseret Biologicals, Inc.
Category: homeopathic | Type: HUMAN OTC DRUG LABEL
Date: 20240423

ACTIVE INGREDIENTS: PORK LIVER 6 [hp_X]/1 mL; HISTAMINE DIHYDROCHLORIDE 6 [hp_X]/1 mL; THUJA OCCIDENTALIS LEAFY TWIG 6 [hp_X]/1 mL; SACCHAROMYCES CEREVISIAE RNA 10 [hp_X]/1 mL; ECHINACEA ANGUSTIFOLIA WHOLE 12 [hp_X]/1 mL; RHODODENDRON TOMENTOSUM LEAFY TWIG 12 [hp_X]/1 mL; DAPHNE MEZEREUM BARK 12 [hp_X]/1 mL; SILICON DIOXIDE 12 [hp_X]/1 mL; INFLUENZA A VIRUS A/VICTORIA/2570/2019 IVR-215 (H1N1) ANTIGEN (UV, FORMALDEHYDE INACTIVATED) 12 [hp_X]/1 mL; INFLUENZA A VIRUS A/DARWIN/9/2021 IVR-228 (H3N2) ANTIGEN (UV, FORMALDEHYDE INACTIVATED) 12 [hp_X]/1 mL; INFLUENZA B VIRUS B/AUSTRIA/1359417/2021 BVR-26 ANTIGEN (UV, FORMALDEHYDE INACTIVATED) 12 [hp_X]/1 mL; INFLUENZA B VIRUS B/PHUKET/3073/2013 ANTIGEN (UV, FORMALDEHYDE INACTIVATED) 12 [hp_X]/1 mL; ANTIMONY POTASSIUM TARTRATE 30 [hp_X]/1 mL; ARSENIC TRIOXIDE 30 [hp_X]/1 mL; BRYONIA ALBA ROOT 30 [hp_X]/1 mL; GELSEMIUM SEMPERVIRENS ROOT 30 [hp_X]/1 mL; HYOSCYAMUS NIGER 30 [hp_X]/1 mL; FELIS CATUS MILK 30 [hp_X]/1 mL; MERCURIUS SOLUBILIS 30 [hp_X]/1 mL; NIACINAMIDE 30 [hp_X]/1 mL; POLYGALA SENEGA ROOT 30 [hp_X]/1 mL; SPIGELIA ANTHELMIA WHOLE 30 [hp_X]/1 mL; SULFUR 30 [hp_X]/1 mL; ZINC 30 [hp_X]/1 mL
INACTIVE INGREDIENTS: WATER; ALCOHOL

DRUG FACTS:

OTC - ACTIVE INGREDIENT SECTION

Hepar Suis 6X, 12X, 18X, 24X, 30X, Histaminum Hydrochloricum 6X, 12X, 18X, 24X, 30X, Thuja Occidentalis 6X, 12X, 18X, 30X, RNA 10X, 12X, 18X, 30X, 60X, 100X, Echinacea 12X, Ledum Palustre 12X, Mezereum 12X, Silicea 12X, 18X, 24X, Influenzinum 12X, 18X, 30X, 60X, 100X, Antimonium Tartaricum 30X, Arsenicum Album 30X, Bryonia 30X, Gelsemium Sempervirens 30X, Hyoscyamus Niger 30X, Lac Felinum 30X, Mercurius Solubilis 30X, Nicotinamidum 30X, Senega Officinalis 30X, Spigelia Anthelmia 30X, Sulphur 30X, Zincum Metallicum 30X.

PURPOSE:

For the temporary relief of after-effects of general vaccinations such as sore muscles, headache and tiredness.**

**These statements are based upon homeopathic principles. They have not been reviewed by the Food and Drug Administration.

WARNINGS:

Keep out of reach of children. In case of overdose, contact a physician or Poison Control Center right away.

If pregnant or breast-feeding, ask a health professional before use.

Tamper seal: "Sealed for Your Protection." Do not use if seal is broken or missing.

KEEP OUT OF REACH OF CHILDREN:

In case of overdose, contact a physician or Poison Control Center right away.

DIRECTIONS:

1-10 drops under the tongue, 3 times a day or as directed by a health professional. Consult a physician for use in children under 12 years of age.

INDICATIONS:

For the temporary relief of after-effects of general vaccinations such as sore muscles, headache and tiredness.**

**These statements are based upon homeopathic principles. They have not been reviewed by the Food and Drug Administration.

INACTIVE INGREDIENTS:

Demineralized Water, 25% Ethanol

QUESTIONS:

Dist. By: Deseret Biologicals, Inc.

469 W. Parkland Drive

Sandy, UT 84070 www.desbio.com

PACKAGE LABEL DISPLAY:

DESBIO

NDC 43742-2087-1

HOMEOPATHIC

VACC:HC

1 FL OZ (30 ml)